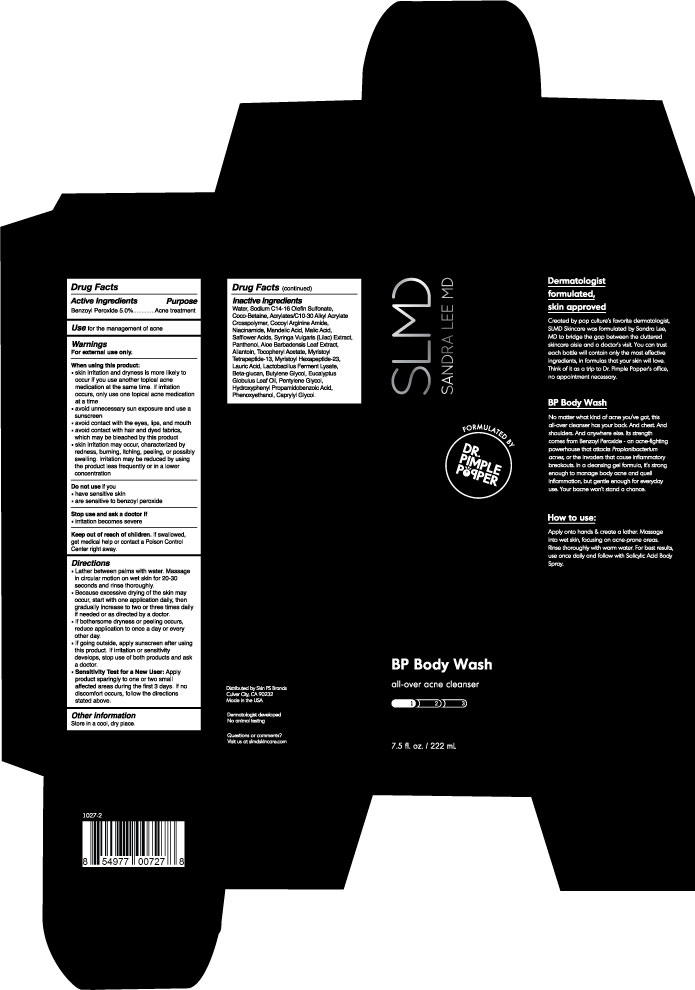 DRUG LABEL: SLMD BP Body Wash
NDC: 59958-406 | Form: GEL
Manufacturer: Owen Biosciences Inc.
Category: otc | Type: HUMAN OTC DRUG LABEL
Date: 20190830

ACTIVE INGREDIENTS: BENZOYL PEROXIDE 5 g/100 g
INACTIVE INGREDIENTS: WATER 70 g/100 g; SODIUM C14-16 OLEFIN SULFONATE 15 g/100 g; COCO-BETAINE 5 g/100 g

Active Ingredients

Benzoyl Peroxide 5.0%

Use

For the management of acne.

Warnings For external use only.

When using this product:
• skin irritation and dryness is more likely to
occur if you use another topical acne
medication at the same time. If irritation
occurs, only use one topical acne medication
at a time.
• avoid unnecessary sun exposure and use a
sunscreen
• avoid contact with the eyes, lips, and mouth
• avoid contact with hair and dyed fabrics,
which may be bleached by this products
• skin irritation may occur, characterized by
redness, burning, itching, peeling, or possibly
swelling. Irritation may be reduced by using
the product less frequently or in a lower
concentration

Do not use if you

• have sensitive skin
• are sensitive to benzoyl peroxide

Stop use and ask a doctor if

•irriatation becomes servere

Keep out of reach of children.

If swallowed, get medical help or
contact a Poison Control Center
right away

Directions

• Lather between palms with water. Massage
in circular motion on wet skin for 20-30
seconds and rinse thoroughly.
• Because excessive drying of the skin may
occur, start with one application daily. Then
gradually increase to two or three times daily
if needed or as directed by a doctor.
• if bothersome dryness or peeling occurs,
reduce application to once a day or every
other day.
• if going outside, apply sunscreen after using
this product. If irritation or sensitivity
develops, stop use of both products and ask
a doctor.
• Sensitivity Test for a New User: Apply
product sparingly to one or two small
affected areas during the first 3 days. If no
discomfort occurs, follow the directions
stated above.

OTHER SAFETY INFORMATION

Store in a cool, dry place.

INACTIVE INGREDIENT

Water, Sodium C14-16 Olefin Sulfonate,
Coco-Betaine, Acrylates/C10-30 Alkyl Acrylate
Crosspolymer, Cocoyl Arginine Amide,
Niacinamide, Mandelic Acid, Malic Acid,
Safflower Acids, Syringa Vulgaris (Lilac) Extract,
Penthenol, Aloe Barbadensis Leaf Extract,
Allantoin, Tocopheryl Acetate, Myristoyl
Tetrapeptide-13, Myristoyl Hexapeptide-23,
Lauric Acid, Lactobacillus Ferment Lysate,
Beta-glucan, Butylene Glycol, Eucalyptus
Globulus Leaf Oil, Pentylene Glycol,
Hydroxyphenyl Propamidobenzoic Acid,
Phenoxyethanol, Caprylyl Glycol.

PURPOSE

For the treatment of Acne

BP Body Wash.jpg